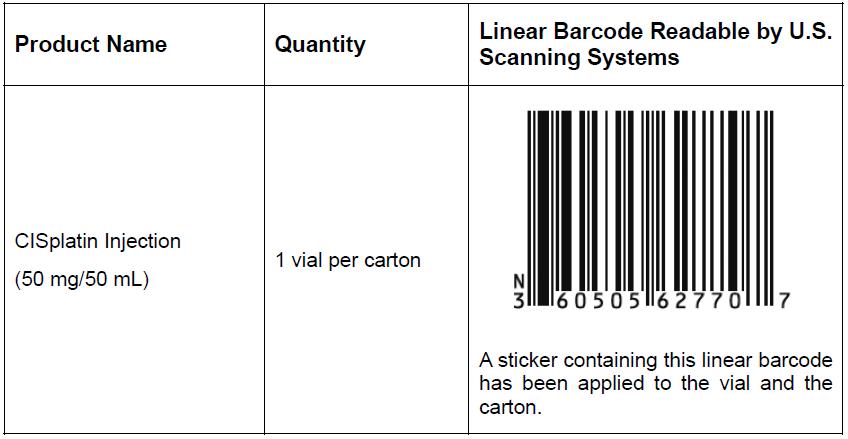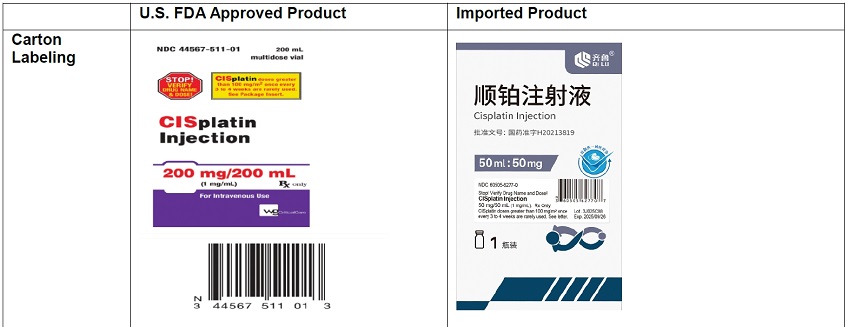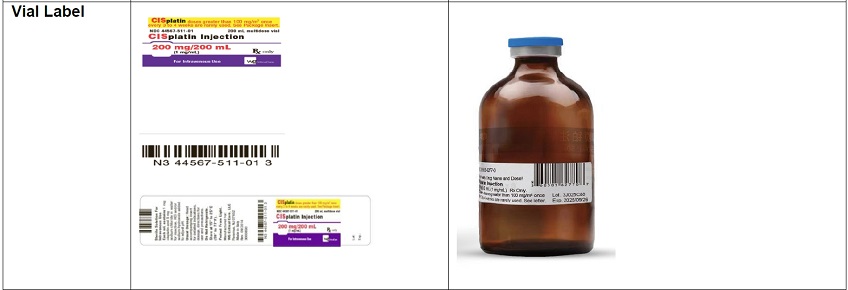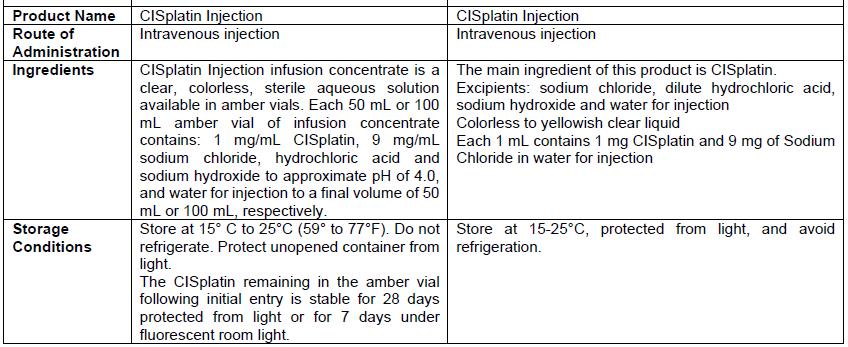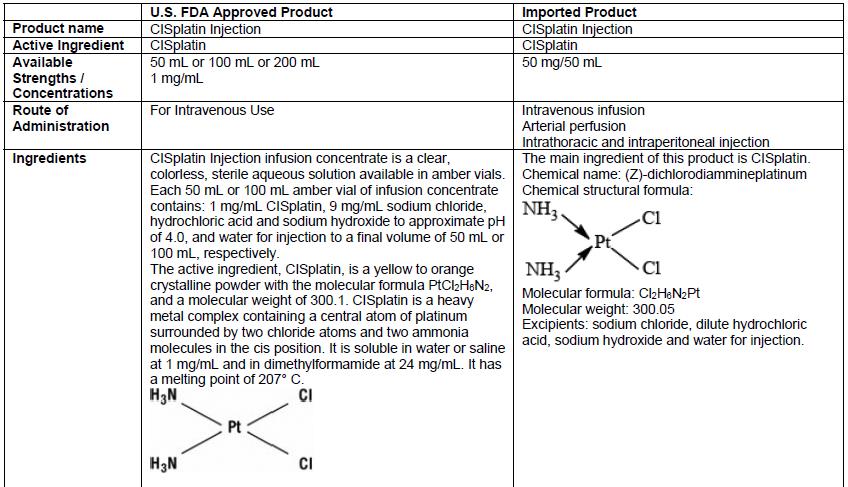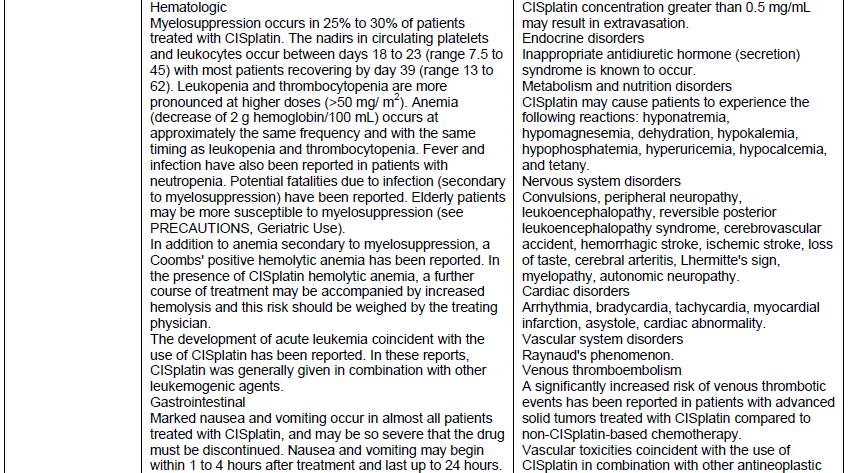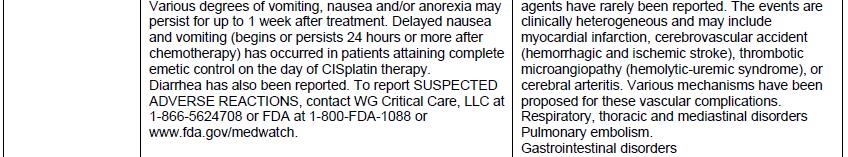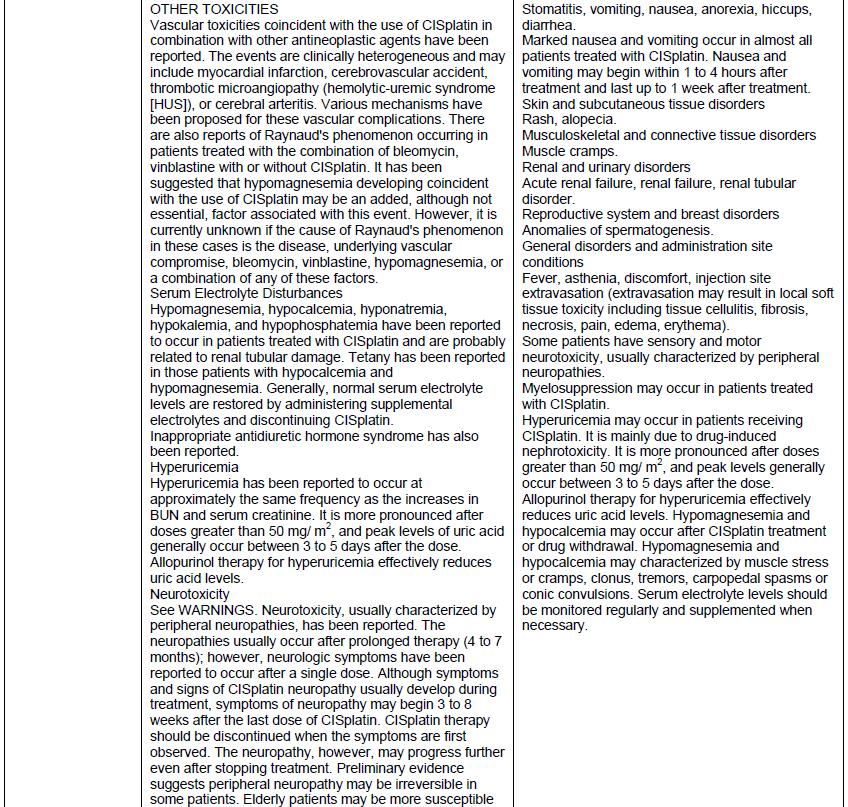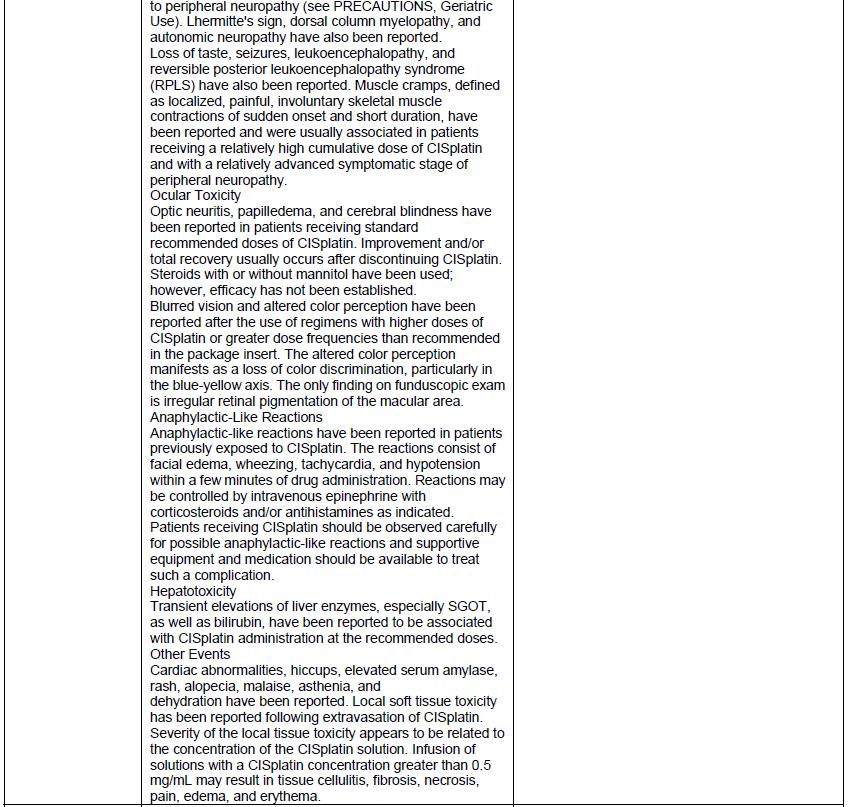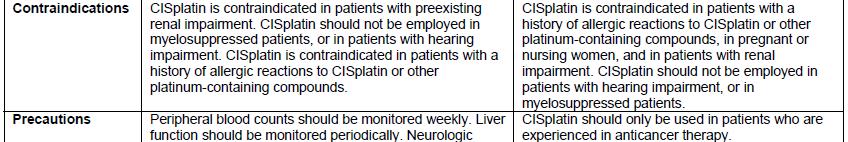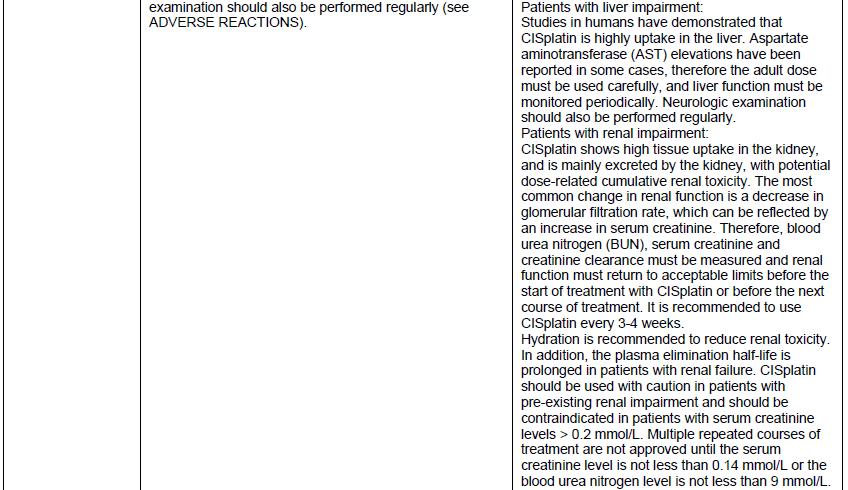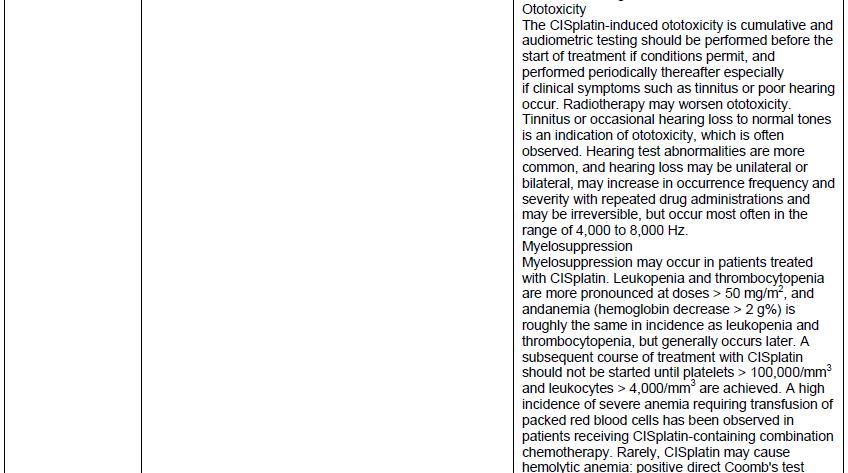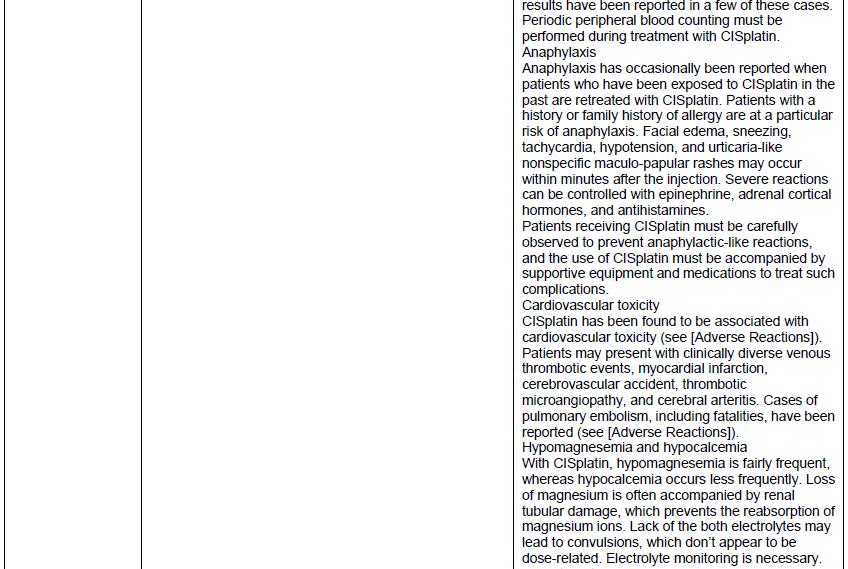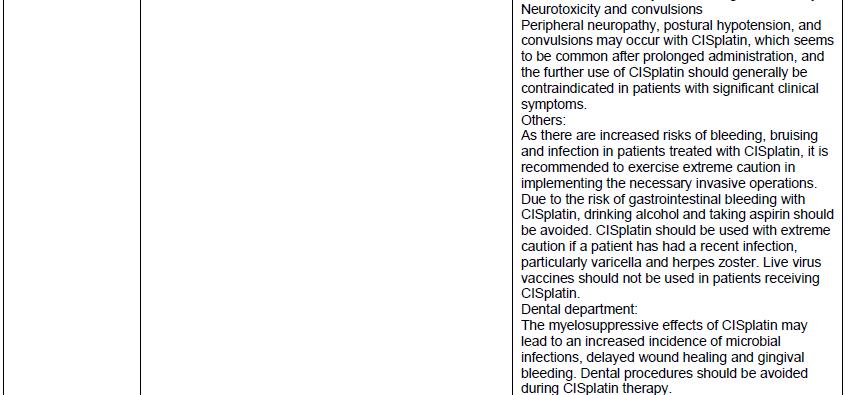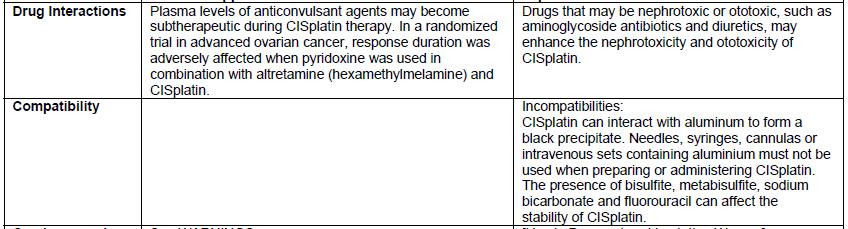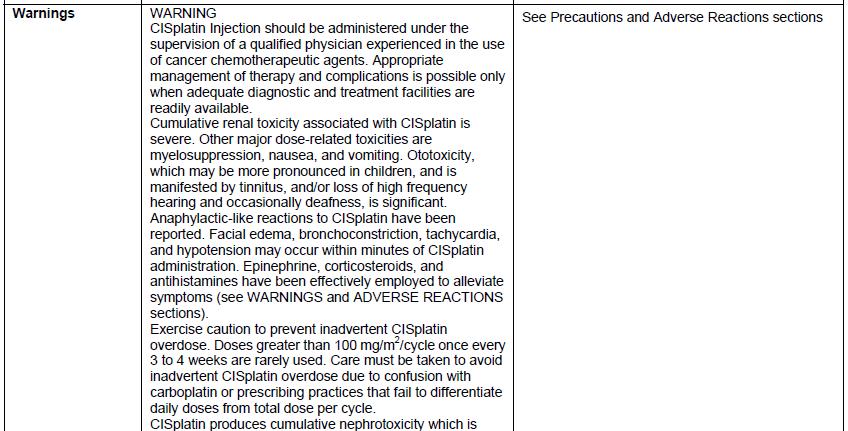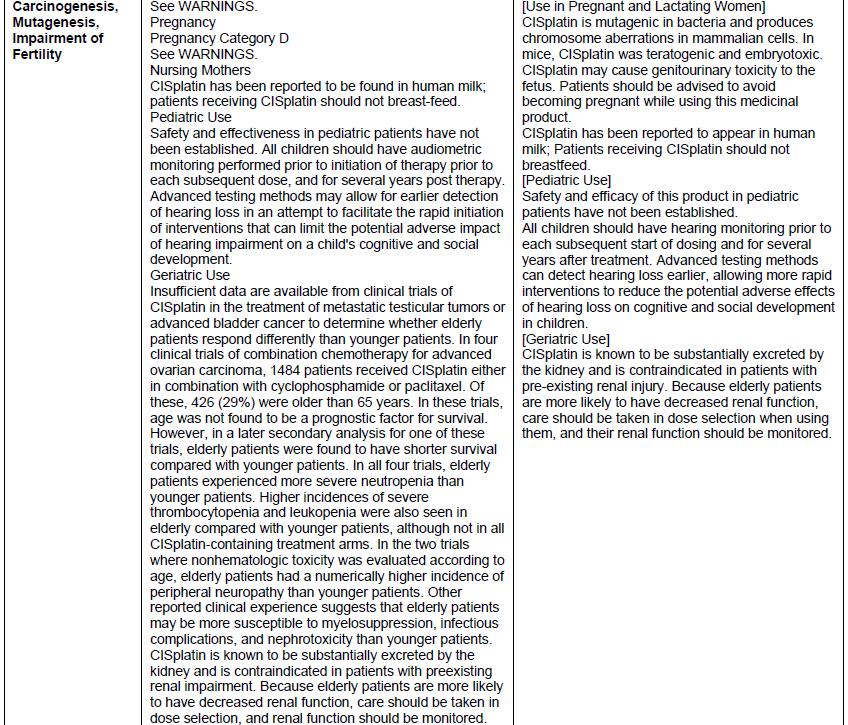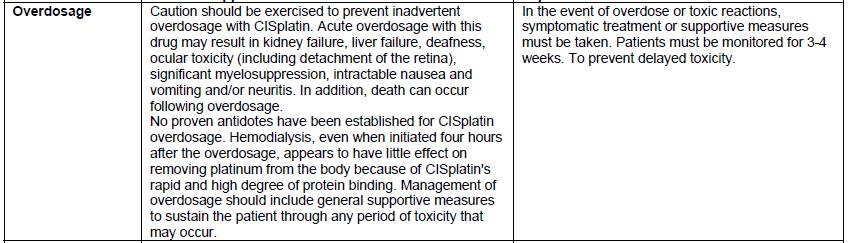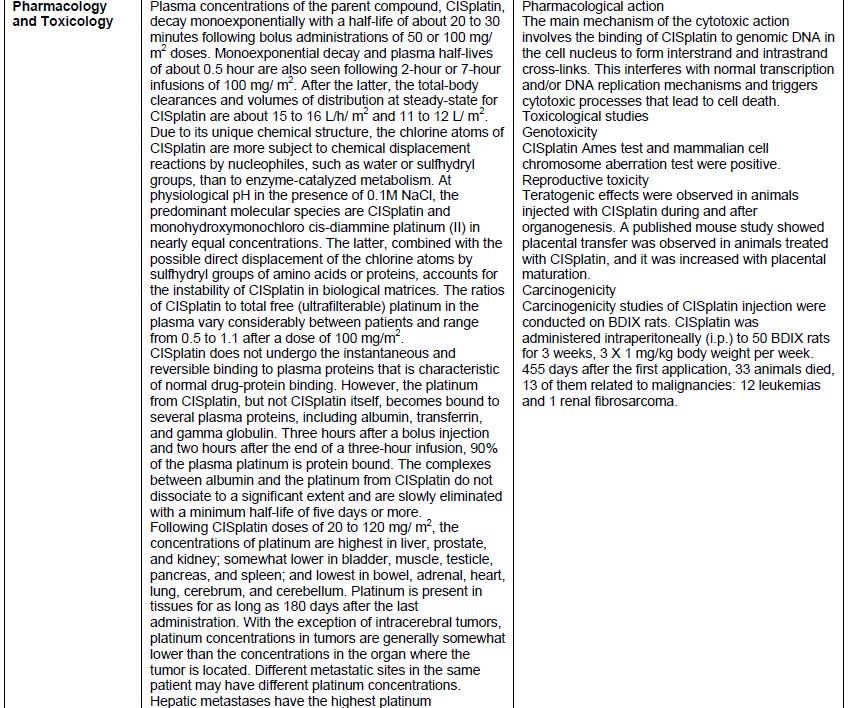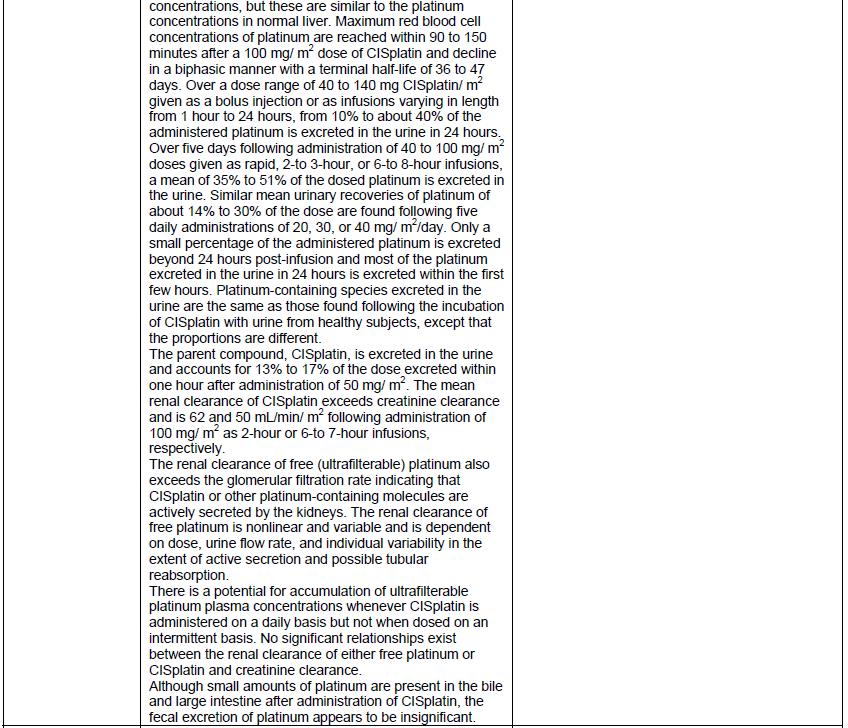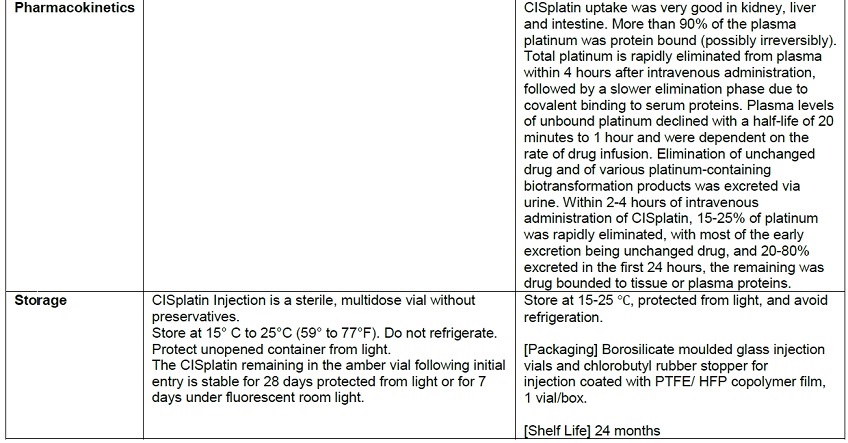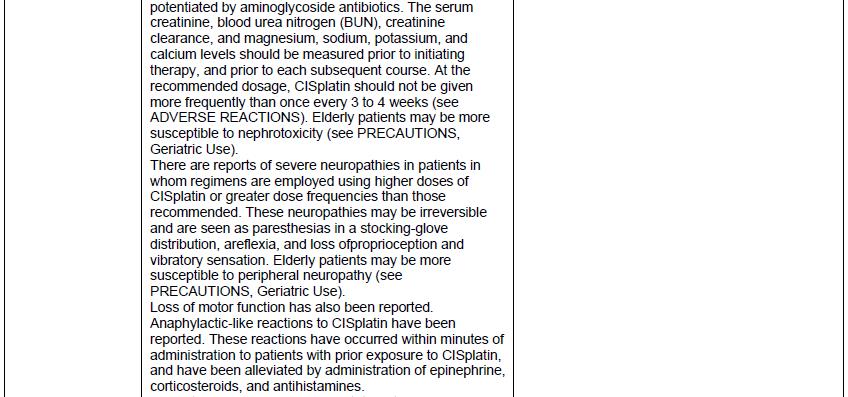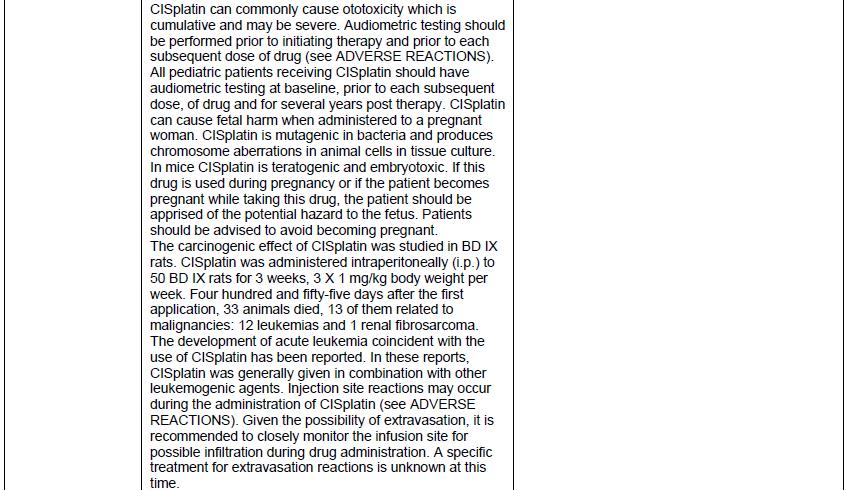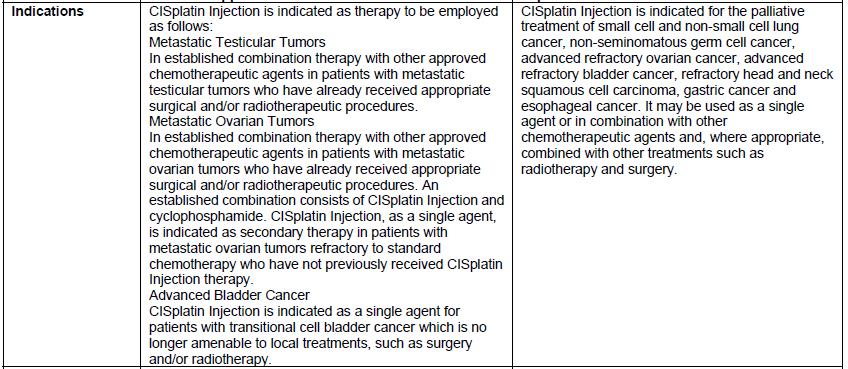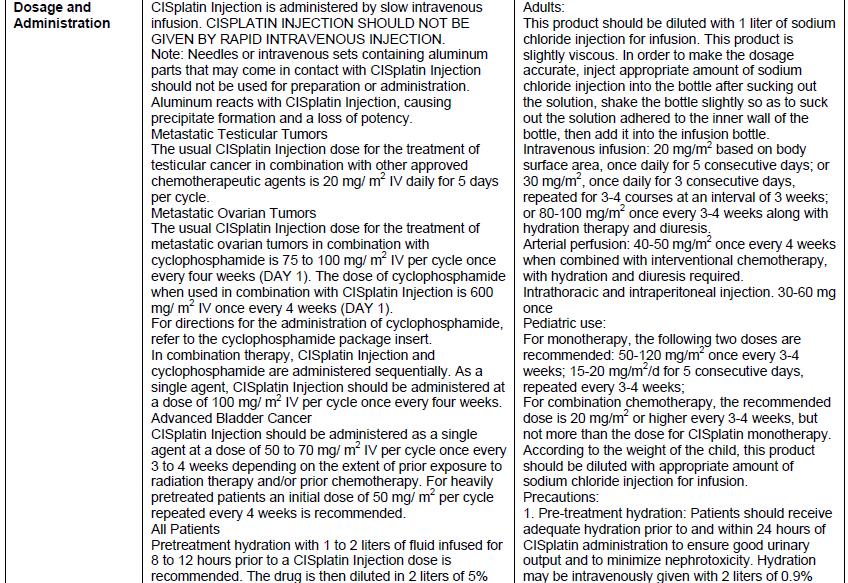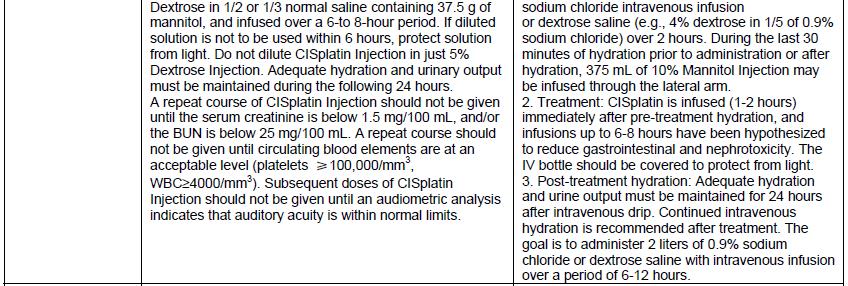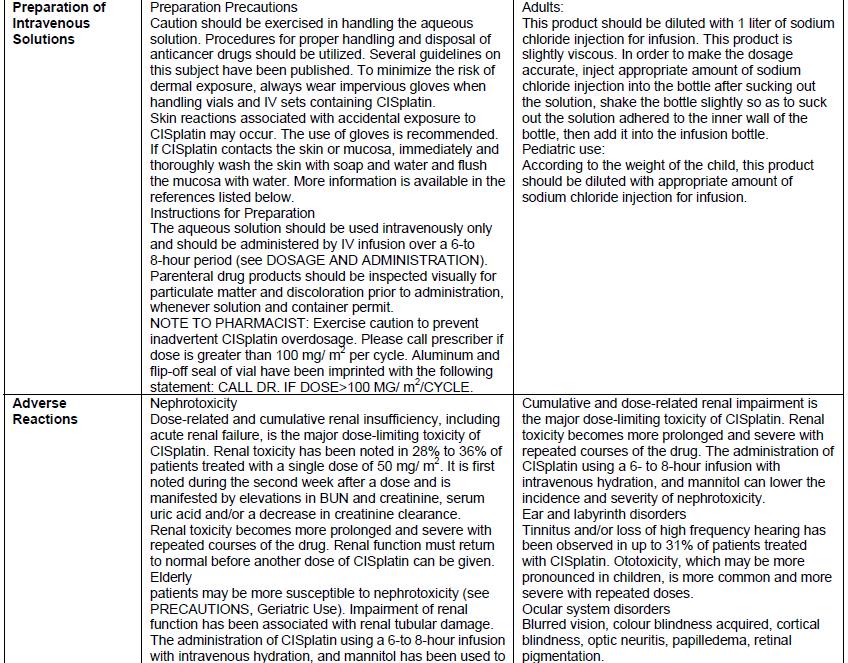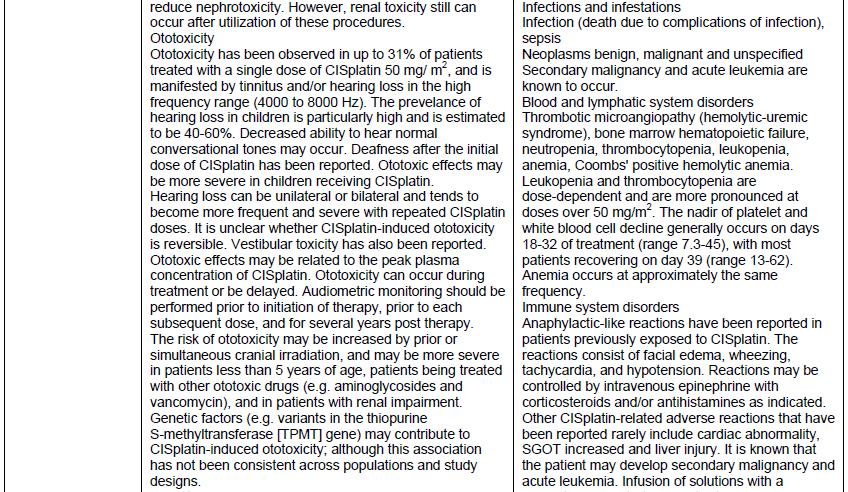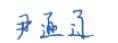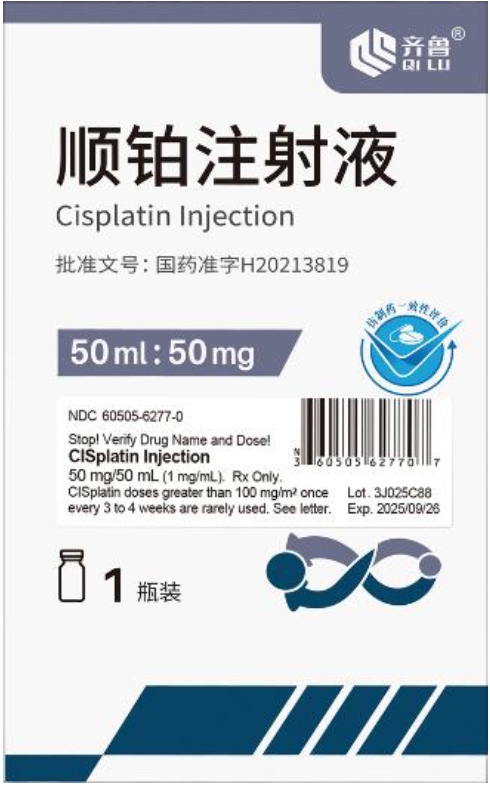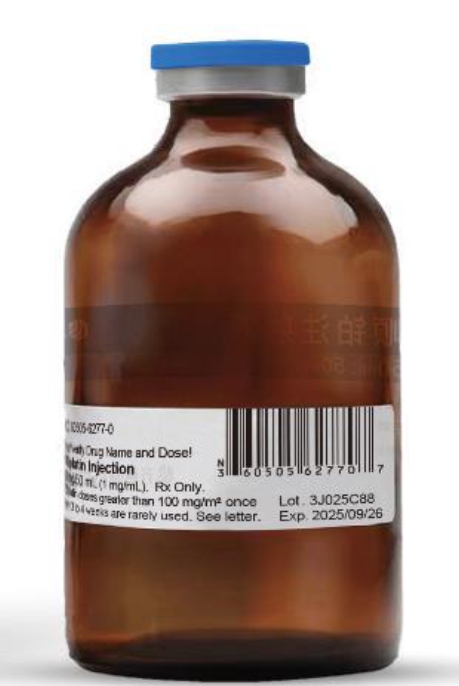 DRUG LABEL: CISplatin
NDC: 60505-6277 | Form: INJECTION, SOLUTION
Manufacturer: Apotex Corp.
Category: prescription | Type: HUMAN PRESCRIPTION DRUG LABEL
Date: 20231221

ACTIVE INGREDIENTS: CISPLATIN 50 mg/50 mL
INACTIVE INGREDIENTS: SODIUM CHLORIDE; HYDROCHLORIC ACID; SODIUM HYDROXIDE; WATER

HEALTH CARE PROVIDER LETTER

IMPORTANT PRESCRIBING INFORMATION

December 6, 2023

Subject: Temporary Importation of CISplatin Injection (50 mg/50 mL) with non-U.S. Labeling to Address Drug Shortage

Dear Healthcare Professional,

Due to the critical shortage of CISplatin Injection in the United States (U.S.), Qilu Pharmaceutical Co. Ltd (Qilu), in conjunction with Apotex Corp., is coordinating with the U.S. Food and Drug Administration (FDA) to increase the availability of the drug. Qilu has initiated temporary importation of CISplatin Injection (50 mg/50 mL) with vial and carton labels in Chinese into the U.S. market. The CISplatin Injection from Qilu is marketed and manufactured in China and is not FDA-approved.

Only Qilu or its distributor, Apotex Corp., is authorized by the FDA to import or distribute Qilu's CISplatin Injection in the United States.

Effective immediately and during this temporary period, Apotex Corp. will distribute the following presentation of CISplatin Injection to address the critical shortage:

Product Name | Quantity | Description | U.S. NDC Number | Lot Number | Expiration Date
CISplatin Injection (50 mg/50 mL) | 1 vial per carton | Colorless to yellowish clear liquid Each 1 mL contains 1 mg of CISplatin and 9 mg of Sodium Chloride in water for injection. | 60505-6277-0 See Appendix 1 for a scannable linear barcode readable by U.S. scanning systems. | 3J025C88 | 2025-09-26
CISplatin Injection (50 mg/50 mL) | 1 vial per carton | Colorless to yellowish clear liquid Each 1 mL contains 1 mg of CISplatin and 9 mg of Sodium Chloride in water for injection. | 60505-6277-0 See Appendix 1 for a scannable linear barcode readable by U.S. scanning systems. | 3J026C88 | 2025-09-26
CISplatin Injection (50 mg/50 mL) | 1 vial per carton | Colorless to yellowish clear liquid Each 1 mL contains 1 mg of CISplatin and 9 mg of Sodium Chloride in water for injection. | 60505-6277-0 See Appendix 1 for a scannable linear barcode readable by U.S. scanning systems. | 3J027C88 | 2025-09-26
CISplatin Injection (50 mg/50 mL) | 1 vial per carton | Colorless to yellowish clear liquid Each 1 mL contains 1 mg of CISplatin and 9 mg of Sodium Chloride in water for injection. | 60505-6277-0 See Appendix 1 for a scannable linear barcode readable by U.S. scanning systems. | 3K028C88 | 2025-10-08
CISplatin Injection (50 mg/50 mL) | 1 vial per carton | Colorless to yellowish clear liquid Each 1 mL contains 1 mg of CISplatin and 9 mg of Sodium Chloride in water for injection. | 60505-6277-0 See Appendix 1 for a scannable linear barcode readable by U.S. scanning systems. | 3K029C88 | 2025-10-08
CISplatin Injection (50 mg/50 mL) | 1 vial per carton | Colorless to yellowish clear liquid Each 1 mL contains 1 mg of CISplatin and 9 mg of Sodium Chloride in water for injection. | 60505-6277-0 See Appendix 1 for a scannable linear barcode readable by U.S. scanning systems. | 3K030C88 | 2025-10-08
CISplatin Injection (50 mg/50 mL) | 1 vial per carton | Colorless to yellowish clear liquid Each 1 mL contains 1 mg of CISplatin and 9 mg of Sodium Chloride in water for injection. | 60505-6277-0 See Appendix 1 for a scannable linear barcode readable by U.S. scanning systems. | 3K031C88 | 2025-10-09
CISplatin Injection (50 mg/50 mL) | 1 vial per carton | Colorless to yellowish clear liquid Each 1 mL contains 1 mg of CISplatin and 9 mg of Sodium Chloride in water for injection. | 60505-6277-0 See Appendix 1 for a scannable linear barcode readable by U.S. scanning systems. | 3K032C88 | 2025-10-09
CISplatin Injection (50 mg/50 mL) | 1 vial per carton | Colorless to yellowish clear liquid Each 1 mL contains 1 mg of CISplatin and 9 mg of Sodium Chloride in water for injection. | 60505-6277-0 See Appendix 1 for a scannable linear barcode readable by U.S. scanning systems. | 3K033C88 | 2025-10-09
CISplatin Injection (50 mg/50 mL) | 1 vial per carton | Colorless to yellowish clear liquid Each 1 mL contains 1 mg of CISplatin and 9 mg of Sodium Chloride in water for injection. | 60505-6277-0 See Appendix 1 for a scannable linear barcode readable by U.S. scanning systems. | 3K034C88 | 2025-10-11
CISplatin Injection (50 mg/50 mL) | 1 vial per carton | Colorless to yellowish clear liquid Each 1 mL contains 1 mg of CISplatin and 9 mg of Sodium Chloride in water for injection. | 60505-6277-0 See Appendix 1 for a scannable linear barcode readable by U.S. scanning systems. | 3K035C88 | 2025-10-11
CISplatin Injection (50 mg/50 mL) | 1 vial per carton | Colorless to yellowish clear liquid Each 1 mL contains 1 mg of CISplatin and 9 mg of Sodium Chloride in water for injection. | 60505-6277-0 See Appendix 1 for a scannable linear barcode readable by U.S. scanning systems. | 3K036C88 | 2025-10-11

It is important to note the following:

- The carton labeling and vial label did not include the warning statements, “Stop! Verify Drug Name and Dose!” or “CISplatin doses greater than 100 mg/m^2once every 3 to 4 weeks are rarely used”. Thus, a sticker containing this warning statement, the name of the product, strength, concentration, U.S. NDC number, Lot number, expiration date, Rx only, and linear barcode has been applied to the vial and the carton.
- The vial label did not have the translated name of the product “CISplatin”. Thus, a sticker containing the information noted in the bullet above has been applied to the vial.
- Incompatible with solutions containing bisulfite, metabisulfite, sodium bicarbonate and fluorouracil.
- The product is colorless to yellowish clear liquid.
- The vial and carton labels will display the text used and approved for marketing the products in China containing Chinese only text. Example images of this labeling are provided in Appendix 2.
- There are differences in the format and content of the labeling between the FDA-approved product and Qilu’s CISplatin Injection. Please see the product comparison table in Appendix 3 and corresponding English translations.
- The labeling for the imported product states that this product is slightly viscous and to achieve an accurate dose, you might need to rinse the vial with sodium chloride injection to remove the solution adhered to the inner wall of the vial.

CISplatin injection is available only by prescription in the U.S. The imported lots did not have the statement “Rx only” on their labeling. This information is included on the sticker noted in the bullet above.

The carton of the imported product does not include a product identifier. Specifically, each package of product does not include the NDC, unique serial number, lot number, and expiration date in both human-readable form and a two-dimensional data matrix barcode.

Please refer to the package insert for the FDA-approved CISplatin Injection drug product for full prescribing information.

Finally, please ensure that your staff and others in your institution who may be involved in the administration of CISplatin Injection receive a copy of this letter and review the information.

If you have any questionsabout the information contained in this letter, any quality related problems, or questions on the use of Qilu’s CISplatin Injection, please contact Apotex Corp. Customer Service at 1-800-706-5575.

For ordering information, please contact your primary wholesaler or distributor to place an order with Apotex Corp. at 1-800-706-5575.

Healthcare providers should report adverse events associated with the use of Qilu’s CISplatin Injection to Apotex Corp. at 1-800-706-5575.

Adverse events or quality problems experienced with the use of this product may also be reported to the FDA’s MedWatch Adverse Event Reporting Program either online, by regular mail, or by fax:

- Complete and submit the report Online: www.fda.gov/medwatch/report.htm
- Regular mail or Fax: Download form www.fda.gov/MedWatch/getforms.htm or call 1-800-332-1088 to request a reporting form, then complete and return to the address on the pre-addressed form or submit by fax to 1-800-FDA-0178 (1-800-332-0178).

We remain at your disposal to answer any questions you may have about our product; and provide more information if needed.

Sincerely,

Mr. Yin Xunliao
Deputy General Manager
Qilu Pharmaceutical Co., Ltd.

Enclosures:
Appendix 1 – Barcodes for Pharmacy Dispensing
Appendix 2 – Product Label and Product Characteristics Side-by-Side Comparison Table
Appendix 3 – Prescribing Information Side-by-Side Comparison Table
Available at www1.apotex.com/us/CISplatin_Injection

Appendix 1: Barcode for Pharmacy Dispensing

Appendix 2: Product Label and Product Characteristics Side-by-Side Comparison Table

Appendix 3: Prescribing Information Side-by-Side Comparison Table (translated from Chinese)

DHCP version: 34040099636B

PACKAGE LABEL

NDC 60505-6277-0

Stop! Verify Drug Name and Dose!

CISplatin Injection

50 mg/50 mL (1 mg/mL). Rx Only.

CISplatin doses greater than 100 mg/m^2 once every 3 to 4 weeks are rarely used. See letter.